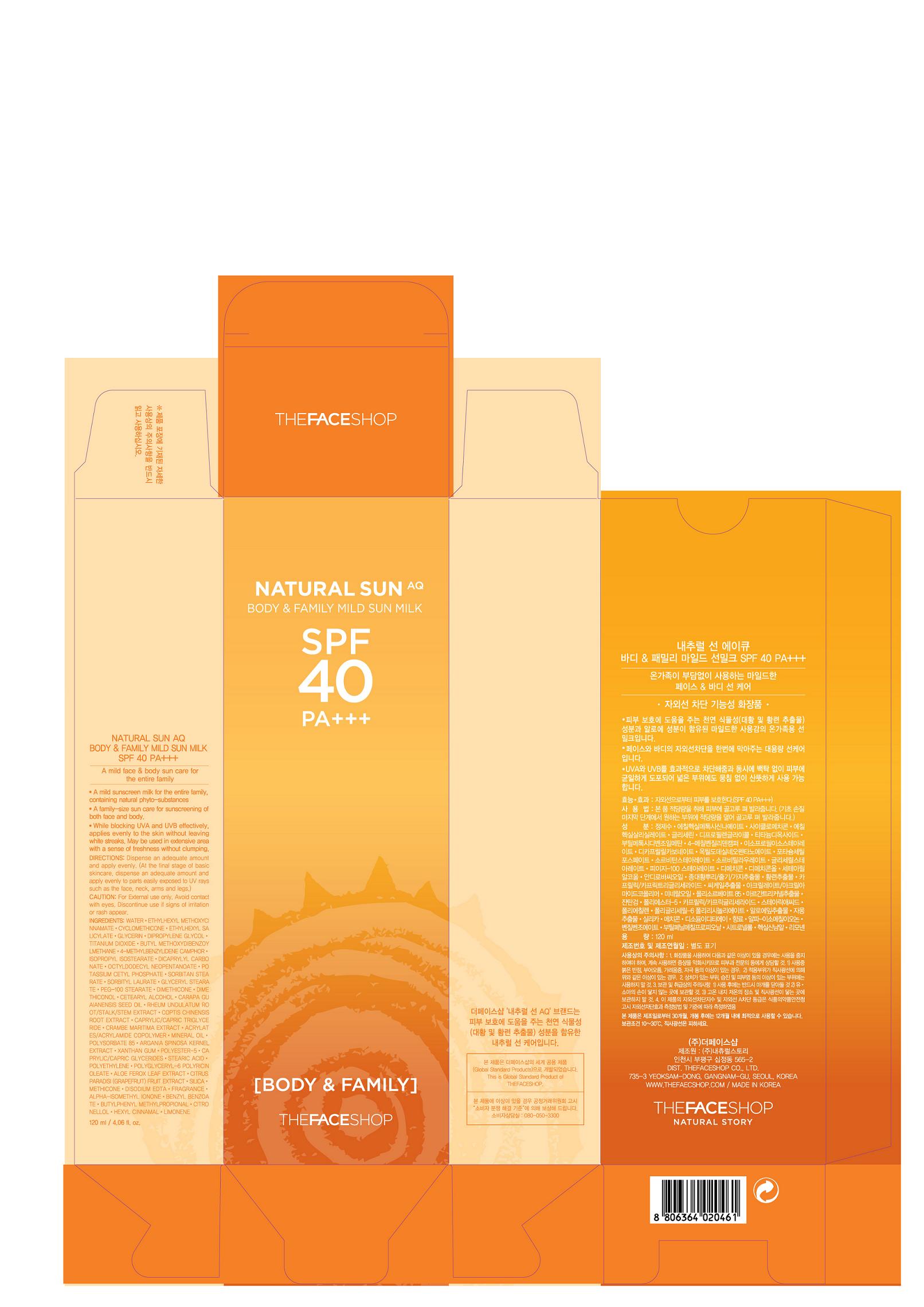 DRUG LABEL: NATURAL SUN AQ BODY AND FAMILY MILD SUN MILK
NDC: 51523-101 | Form: CREAM
Manufacturer: THEFACESHOP CO., LTD
Category: otc | Type: HUMAN OTC DRUG LABEL
Date: 20101129

ACTIVE INGREDIENTS: OCTINOXATE 7.5 mL/100 mL; OCTISALATE 3 mL/100 mL; TITANIUM DIOXIDE 2.34 mL/100 mL; AVOBENZONE 2.3 mL/100 mL; ENZACAMENE 2 mL/100 mL
INACTIVE INGREDIENTS: WATER; CYCLOMETHICONE; GLYCERIN; DIPROPYLENE GLYCOL; DICAPRYLYL CARBONATE; OCTYLDODECYL NEOPENTANOATE; POTASSIUM CETYL PHOSPHATE; SORBITAN MONOSTEARATE; GLYCERYL MONOSTEARATE; POLYOXYL 100 STEARATE; DIMETHICONE; CETOSTEARYL ALCOHOL; .ALPHA.-HEXYLCINNAMALDEHYDE; MINERAL OIL; XANTHAN GUM; STEARIC ACID; EDETATE DISODIUM; BENZYL BENZOATE; BUTYLPHENYL METHYLPROPIONAL

Drug Facts

ACTIVE INGREDIENT

OCTINOXATE (7.50%)
OCTISALATE (3.00%)
TITANIUM DIOXIDE (2.34%)
AVOBENZONE (2.30%)
ENZACAMENE (2.00%)

INACTIVE INGREDIENT

WATER · CYCLOMETHICONE · GLYCERIN · DIPROPYLENE GLYCOL · DICAPRYLYL CARBONATE · OCTYLDODECYL NEOPENTANOATE · POTASSIUM CETYL PHOSPHATE · SORBITAN MONOSTEARATE · GLYCERYL MONOSTEARATE · POLYOXYL 100 STEARATE · DIMETHICONE · CETEARYL ALCOHOL · COPTIS · MINERAL OIL ·XANTHAN GUM · STEARIC ACID · ALOE FEROX LEAF · SILICON DIOXIDE · EDETATE DISODIUM · IONONE · BENZYL BENZOATE · BUTYLPHENYL METHYLPROPIONAL · .ALPHA.-HEXYLCINNAMALDEHYDE

PURPOSE

Face and Body Sun Block.

WHEN USING

Avoid contact with eyes.

STOP USE

Discontinue use if sign of irritation or rash appear.

DOSAGE AND ADMINISTRATION

Dispense an adequate amount and apply evenly. (At the final stage of basic skincare, dispense an adequate amount and apply evenly to parts easily exposed to UV rays such as the face, neck, arms and legs)

PACKAGE LABEL

NATURAL SUN AQ BODY AND FAMILY MILD SUN MILK